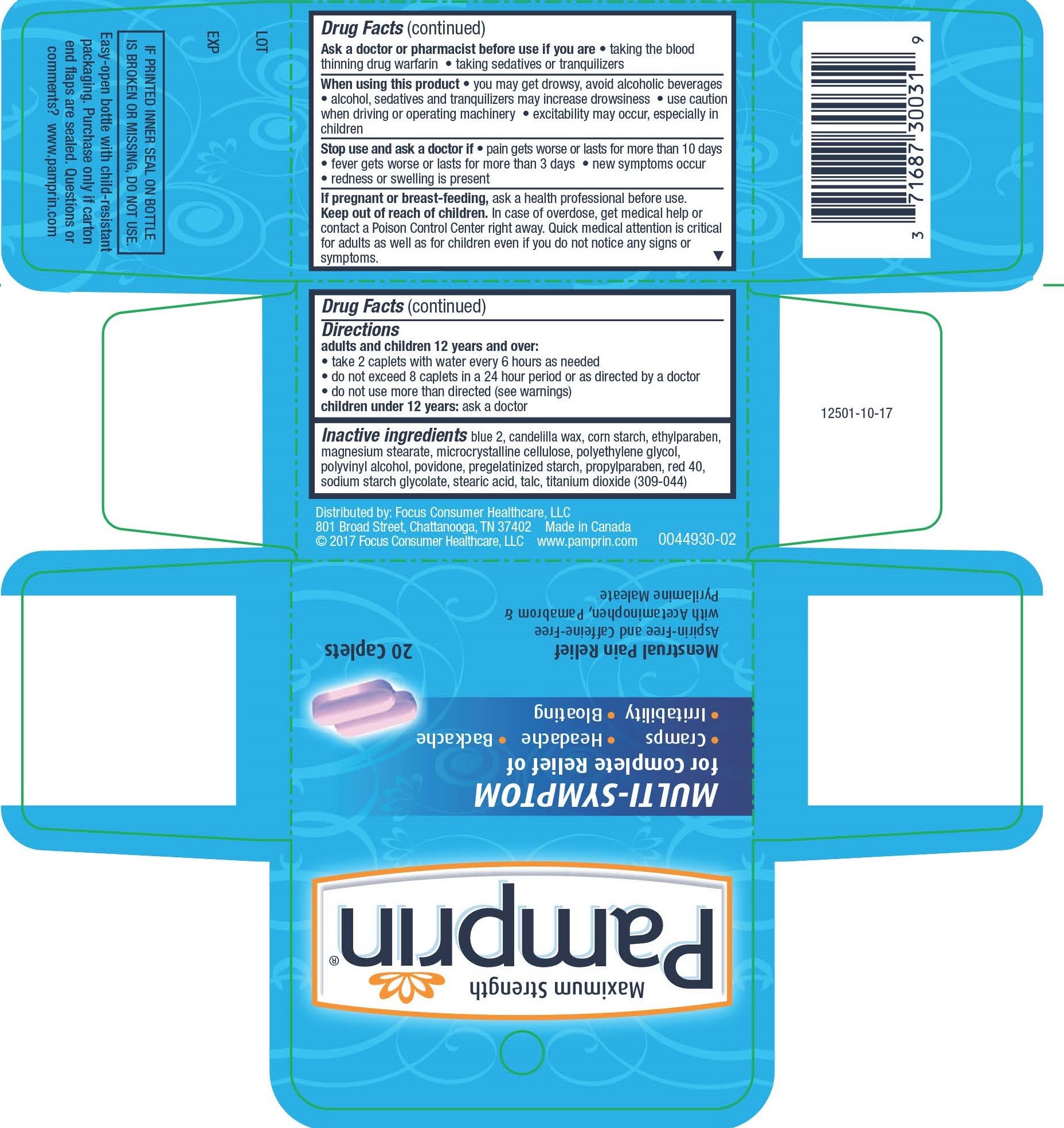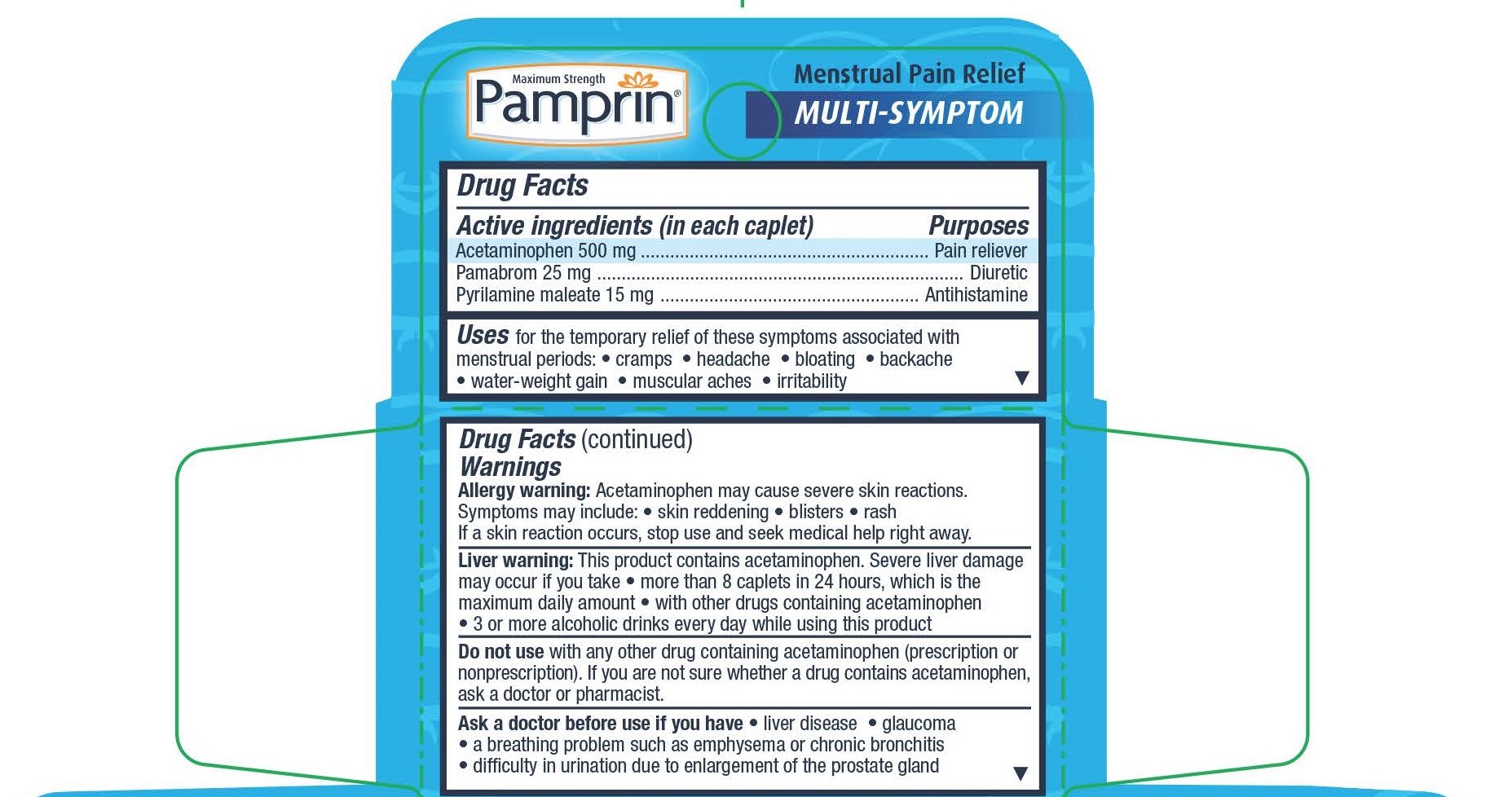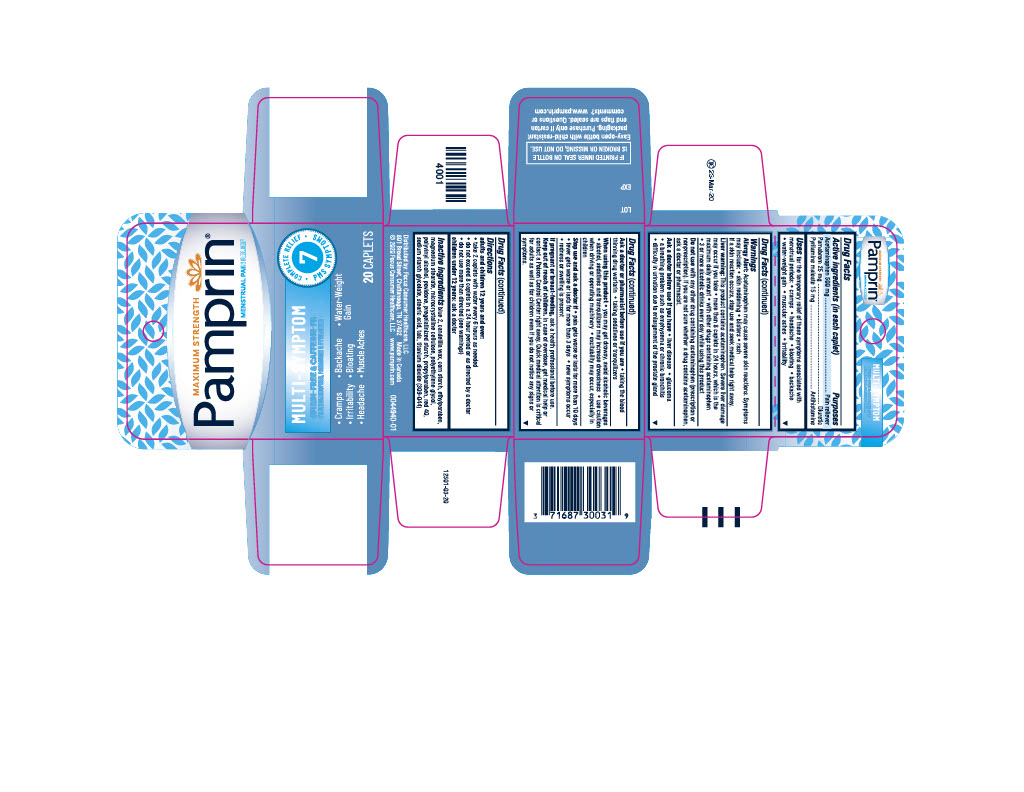 DRUG LABEL: Pamprin Multi-Symptom
NDC: 71687-3003 | Form: TABLET
Manufacturer: Focus Consumer Healthcare, LLC
Category: otc | Type: HUMAN OTC DRUG LABEL
Date: 20250414

ACTIVE INGREDIENTS: PYRILAMINE MALEATE 15 mg/1 1; PAMABROM 25 mg/1 1; ACETAMINOPHEN 500 mg/1 1
INACTIVE INGREDIENTS: ETHYLPARABEN; PROPYLPARABEN; MAGNESIUM STEARATE; MICROCRYSTALLINE CELLULOSE; POLYVINYL ALCOHOL, UNSPECIFIED; FD&C RED NO. 40; POLYETHYLENE GLYCOL, UNSPECIFIED; FD&C BLUE NO. 2; CANDELILLA WAX; STARCH, CORN; POVIDONE, UNSPECIFIED; STEARIC ACID; TALC; SODIUM STARCH GLYCOLATE TYPE A POTATO; TITANIUM DIOXIDE

Pamprin MultiSymptom

Drug Facts

Active ingredients (in each caplet)

Acetaminophen 500 mg
Pamabrom 25 mg
Pyrilamine maleate 15 mg

Purposes

Pain reliever
Diuretic
Antihistamine

INDICATIONS AND USAGE

Uses for the temporary relief of these symptoms associated with menstrual periods:

• cramps

• headache

• bloating

• backache
• water-weight gain

• muscular aches

• irritability

WARNINGS

Allergy warning: Acetaminophen may cause severe skin reactions. Symptoms may include: • skin reddening • blisters • rash

If a skin reaction occurs, stop use and seek medical help right away.

Liver warning: This product contains acetaminophen. Severe liver damage may occur if you take • more than 8 caplets in 24 hours, which is the maximum daily amount • with other drugs containing acetaminophen • 3 or more alcoholic drinks every day while using this product

Do not use with any other drug containing acetaminophen (prescription or nonprescription). If you are not sure whether a drug contains acetaminophen, ask a doctor or pharmacist.

Ask a doctor before use if you have • liver disease • glaucoma • a breathing problem such as emphysema or chronic bronchitis • difficulty in urination due to enlargement of the prostate gland

Ask a doctor or pharmacist before use if you are • taking the blood thinning drug warfarin • taking sedatives or tranquilizers

When using this product • you may get drowsy, avoid alcoholic beverages • alcohol, sedatives and tranquilizers may increase drowsiness • use caution when driving or operating machinery • excitability may occur, especially in children

Stop use and ask a doctor if

• pain gets worse or lasts for more than 10 days
• fever gets worse or lasts for more than 3 days
• new symptoms occur
• redness or swelling is present

PREGNANCY OR BREAST FEEDING

If pregnant or breast-feeding, ask a health professional before use.

Keep out of reach of children.

OVERDOSAGE

In case of overdose, get medical help or contact a Poison Control Center right away. Quick medical attention is critical for adults as well as for children even if you do not notice any signs or symptoms.

Directions

adults and children 12 years and over:

• take 2 caplets with water every 6 hours as needed

• do not exceed 8 caplets in a 24 hour period or as directed by a doctor

• do not use more than directed (see warnings)

children under 12 years: ask a doctor

INACTIVE INGREDIENT

blue 2, candelilla wax, corn starch, ethylparaben, magnesium stearate, microcrystalline cellulose, polyethylene glycol, polyvinyl alcohol, povidone, pregelatinized starch, propylparaben, red 40, sodium starch glycolate, stearic acid, talc, titanium dioxide

Questions or Comments?

www.pamprin.com

IF IMPRINTED INNER SEAL ON BOTTLE IS BROKEN OR MISSING, DO NOT USE.

Easy-open bottle with child-resisitant packaging. Purchase only if carton end flaps are sealed.

Distributed by:

Focus Consumer Healthcare, LLC

801 Broad Street, Chattanooga, TN 37402

Made in Canada

©2017 Focus Consumer Healthcare, LLC

www.pamprin.com

PACKAGE LABEL

Maximum Strength

Pamprin Multi-Symptom

for complete Relief of • Cramps •Headache •Backache •Irritability •Bloating

Mentrual Pain Relief

Aspirin-free and Caffeine-free with Acetaminophen, Pamabrom and Pyrilamine Maleate

20 Caplets